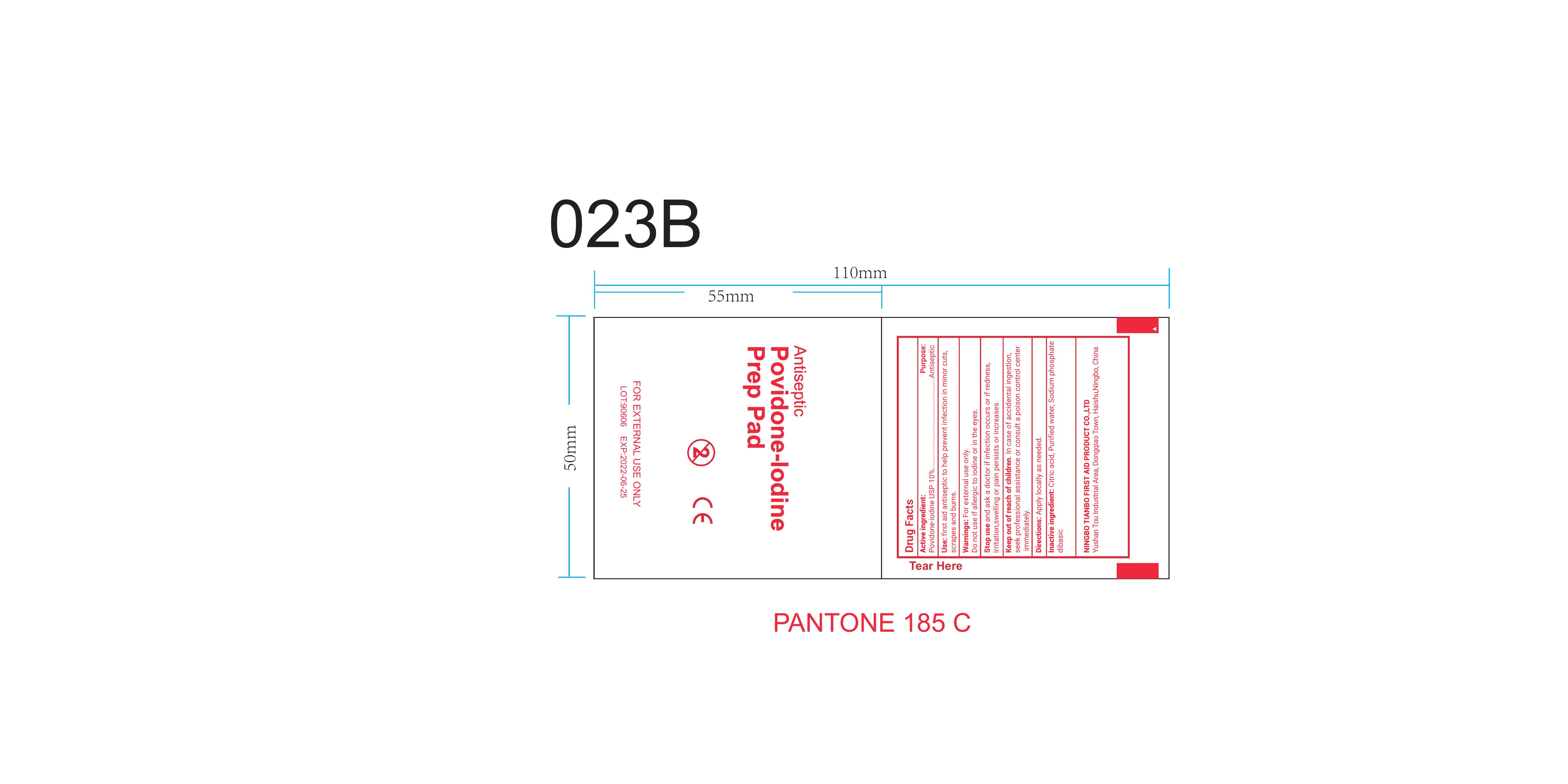 DRUG LABEL: Povidone Iodine Prep Pad
NDC: 73288-002 | Form: SOLUTION
Manufacturer: NINGBO TIANBO FIRST AID PRODUCT CO., LTD.
Category: otc | Type: HUMAN OTC DRUG LABEL
Date: 20260112

ACTIVE INGREDIENTS: POVIDONE-IODINE 1 g/100 g
INACTIVE INGREDIENTS: CITRIC ACID MONOHYDRATE; SODIUM PHOSPHATE, DIBASIC; WATER

73288-002

Active Ingredient: Povidone-Iodine USP (10%)

Purpose: Antiseptic

Use:

First aid antiseptic to help prevent infection in minor cuts, scrapes and burns.

Warnings:

For external use only

Do not use if allergic to iodine or in the eyes

Keep out of reach of children. In case of accidental ingestion, seek professional assistance or consult a poison control center immediately

Stop use and ask a doctor if infection occurs or if redness, irritation, swelling, or pain persists or increases

DOSAGE AND ADMINISTRATION

Apply locally as need

Inactive Ingredient

Citric acid, purified water, Sodium phosphate dibasic